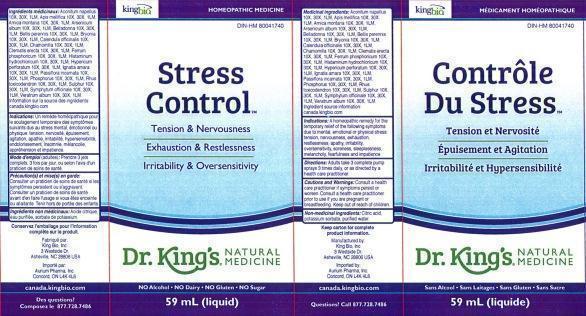 DRUG LABEL: Stress Control / Controle Du Stress
NDC: 57955-1805 | Form: LIQUID
Manufacturer: King Bio Inc.
Category: homeopathic | Type: HUMAN OTC DRUG LABEL
Date: 20140821

ACTIVE INGREDIENTS: ACONITUM NAPELLUS 10 [hp_X]/59 mL; APIS MELLIFERA 10 [hp_X]/59 mL; ARNICA MONTANA 10 [hp_X]/59 mL; ARSENIC TRIOXIDE 10 [hp_X]/59 mL; ATROPA BELLADONNA 10 [hp_X]/59 mL; BELLIS PERENNIS 10 [hp_X]/59 mL; BRYONIA ALBA ROOT 10 [hp_X]/59 mL; CALENDULA OFFICINALIS FLOWERING TOP 10 [hp_X]/59 mL; MATRICARIA RECUTITA 10 [hp_X]/59 mL; CLEMATIS RECTA FLOWERING TOP 10 [hp_X]/59 mL; FERROSOFERRIC PHOSPHATE 10 [hp_X]/59 mL; HISTAMINE DIHYDROCHLORIDE 10 [hp_X]/59 mL; HYPERICUM PERFORATUM 10 [hp_X]/59 mL; STRYCHNOS IGNATII SEED 10 [hp_X]/59 mL; PASSIFLORA INCARNATA FLOWERING TOP 10 [hp_X]/59 mL; PHOSPHORUS 10 [hp_X]/59 mL; TOXICODENDRON PUBESCENS LEAF 10 [hp_X]/59 mL; SULFUR 10 [hp_X]/59 mL; COMFREY ROOT 10 [hp_X]/59 mL; VERATRUM ALBUM ROOT 10 [hp_X]/59 mL
INACTIVE INGREDIENTS: CITRIC ACID MONOHYDRATE; POTASSIUM SORBATE; WATER

Stress Control / Contrôle Du Stress

ACTIVE INGREDIENT

Medicinal ingredients/Ingrédients médicinaux: Aconitum napellus 10X, 30X, 1LM, Apis mellifica 10X, 30X, 1LM, Arnica montana 10X, 30X, 1LM, Arsenicum album 10X, 30X, 1LM, Belladonna 10X, 30X, 1LM, Bellis perennis 10X, 30X, 1LM, Bryonia 10X, 30X, 1LM, Calendula officinalis 10X, 30X, 1LM, Chamomilla 10X, 30X, 1LM, Clematis erecta 10X, 30X, 1LM, Ferrum phosphoricum 10X, 30X, 1LM, Histaminum hydrochloricum 10X, 30X, 1LM, Hypericum perforatum 10X, 30X, 1LM, Ignatia amara 10X, 30X, 1LM, Passiflora incarnata 10X, 30X, 1LM, Phosphorus 10X, 30X, 1LM, Rhus toxicodendron 10X, 30X, 1LM, Sulphur 10X, 30X, 1LM, Symphytum officinale 10X, 30X, 1LM, Veratrum album 10X, 30X, 1LM. Ingredient source information sur la source des ingrédients: canada.kingbio.com

INACTIVE INGREDIENT

Non-medicinal ingredients: Citric acid, potassium sorbate, purified water.

Ingrédients non médicinaux: Acide citrique, eau purifiée, sorbate de potassium.

PURPOSE

Indications: A homeopathic remedy for the temporary relief of the following symptoms due to mental, emotional or physical stress: tension, nervousness, exhaustion, restlessness, apathy, irritability, oversensitivity, soreness sleeplessness, melancholy, fearfulness and impatience.

Indications: un remde homéopathique pour le soulagement temporaire des symptômes suivants dus au stress mental, émotionnel ou physique: tension, nervosité, épuisement, agitation, apathie, irritabilité, hypersensibilité, endolorissement, insomnie, mélancolie, appréhension et impatience.

DOSAGE AND ADMINISTRATION

Directions: Adults: Take 3 complete pump sprays, 3 times daily, or as directed by a health care practitioner.

Mode d'emploi (adultes):Prendre 3 jets complets, 3 fois par joir, ou selon l'avis d'un praticien de soins de santé

INDICATIONS AND USAGE

Indications: A homeopathic remedy for the temporary relief of the following symptoms due to mental, emotional or physical stress:

- tension
- nervousness
- exhaustion
- restlessness
- apathy
- irritability
- oversensitivity
- soreness
- sleeplessness
- melancholy
- fearfulness
- impatience

Indications: un remède homéopathique pour le soulagement temporaire des symptômes suivants dus au stress mental, émotionnel ou physique:

- tension
- nervosité
- épuisement
- agitation
- apathie
- irritabilité
- hypersensibilité
- endolorissement
- insomnie
- mélancolie
- appréhension et impatience

WARNINGS

Cautions and Warnings: Consult a health care practitioner if symptoms persist or worsen. Consult a health care practitioner prior to use if you are pregnant or breastfeeding.

Précaution(s) et mise(s) en garde: Consulter un praticien de soins de santé si les symptômes persistent ou s'aggravent. Consulter un praticien de soins de santé avant d'en faire l'usage si vous êtes enceinte ou allaitante.

Keep out of reach of Children.

Tenir hors de portée des enfants.